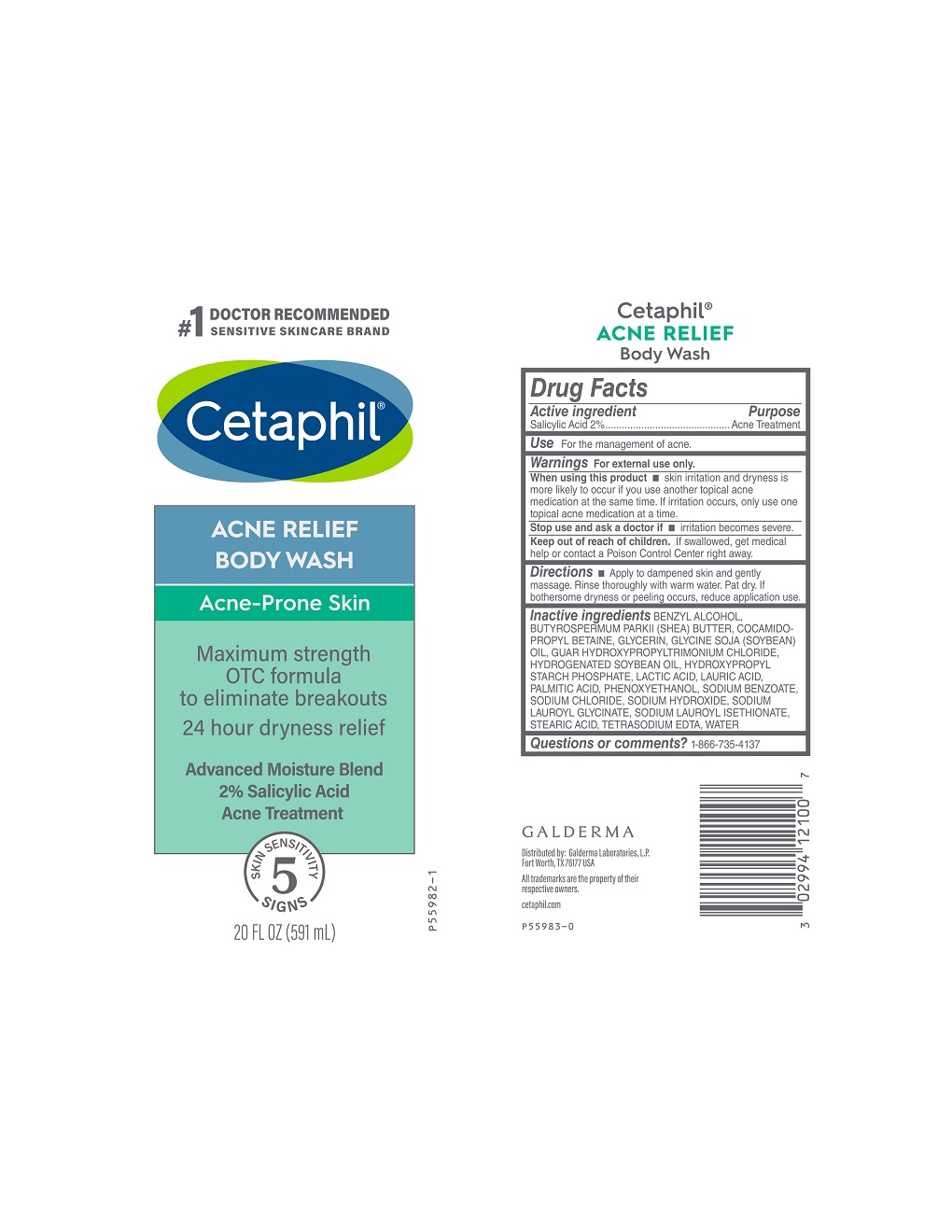 DRUG LABEL: Cetaphil Acne Relief Body Wash
NDC: 0299-4121 | Form: GEL
Manufacturer: Galderma Laboratories, L.P.
Category: otc | Type: HUMAN OTC DRUG LABEL
Date: 20231120

ACTIVE INGREDIENTS: Salicylic Acid 20 mg/1 mL
INACTIVE INGREDIENTS: Benzyl Alcohol; Shea Butter; Cocamidopropyl Betaine; Glycerin; Soybean Oil; Guar Hydroxypropyltrimonium Chloride (1.7 Substituents Per Saccharide); Hydrogenated Soybean Oil; Lactic Acid, Unspecified Form; Lauric Acid; Palmitic Acid; Phenoxyethanol; Sodium Benzoate; Sodium Chloride; Sodium Hydroxide; Sodium Lauroyl Glycinate; Sodium Lauroyl Isethionate; Stearic Acid; Edetate Sodium; Water

Drug Facts

Active Ingredient

Salicylic Acid 2%

Purpose

Acne Treatment

Use

For the management of acne

Warnings

For external use only

When using this product

• skin irritation and dryness is more likely to occur if you use another topical acne medication at the same time. If irritation occurs, only use one topical acne medication at a time.

Stop use and ask a doctor if

• irritation becomes severe.

Keep out of reach of children.

If swallowed, get medical help or contact a Poison Control Center right away.

Directions

Apply to dampened skin and gently massage. Rinse thoroughly with warm water. Pat dry. If bothersome dryness or peeling occurs, reduce application use.

Inactive Ingredients

BENZYL ALCOHOL, BUTYROSPERMUM PARKII (SHEA) BUTTER, COCAMIDOPROPYL BETAINE, GLYCERIN, GLYCINE SOJA (SOYBEAN) OIL, GUAR HYDROXYPROPYLTRIMONIUM CHLORIDE, HYDROGENATED SOYBEAN OIL, HYDROXYPROPYL STARCH PHOSPHATE, LACTIC ACID, LAURIC ACID, PALMITIC ACID, PHENOXYETHANOL, SODIUM BENZOATE, SODIUM CHLORIDE, SODIUM HYDROXIDE, SODIUM LAUROYL GLYCINATE, SODIUM LAUROYL ISETHIONATE, STEARIC ACID, TETRASODIUM EDTA, WATER

Distributed by: Galderma Laboratories, L.P.
Fort Worth, TX 76177 USA
cetaphil.com

PRINCIPAL DISPLAY PANEL - 20 FL OZ bottle

#1 Doctor Recommended
Sensitive Skincare Brand
Cetaphil®

ACNE RELIEF
BODY WASH

Acne-Prone Skin

Maximum strength
OTC formula
to eliminate breakouts

24 hour dryness relief
Advanced Moisture Blend
2% Salicylic Acid
Acne Treatment

5 skin sensitivity signs
20 FL OZ (591 mL)
P55982-1